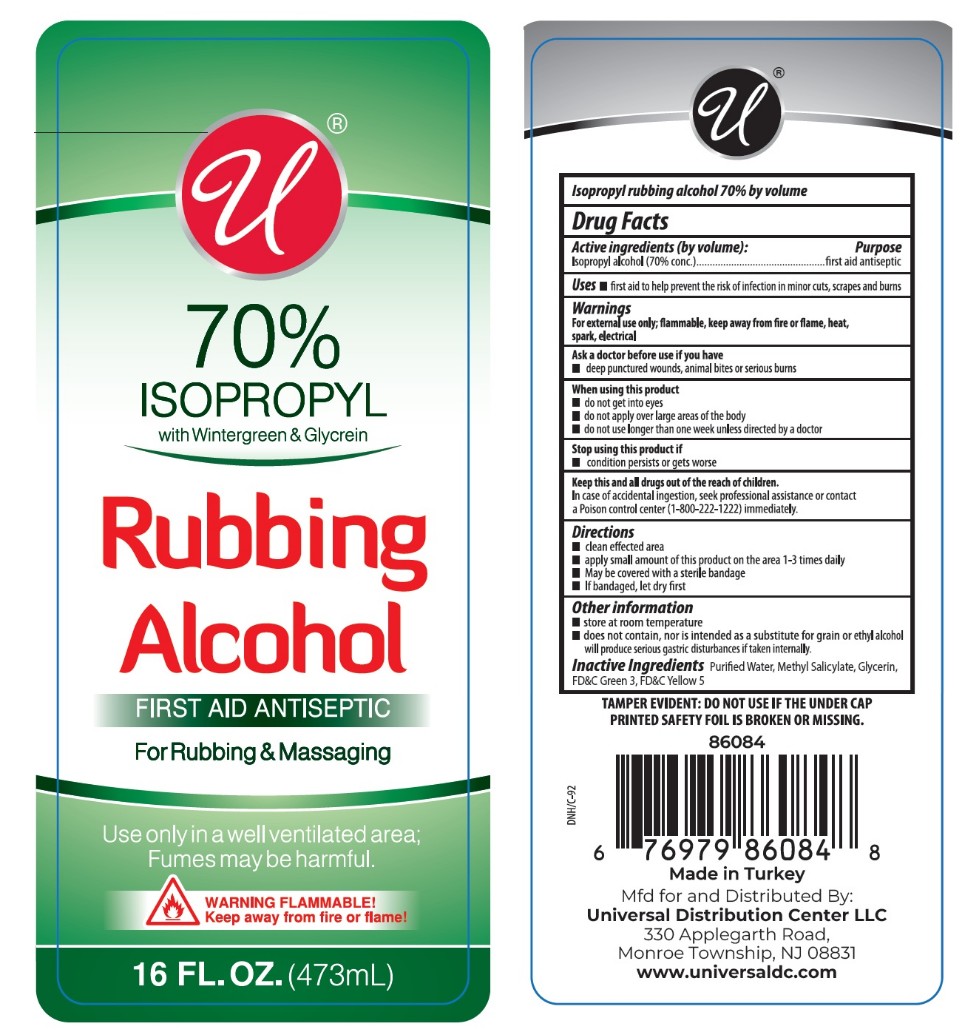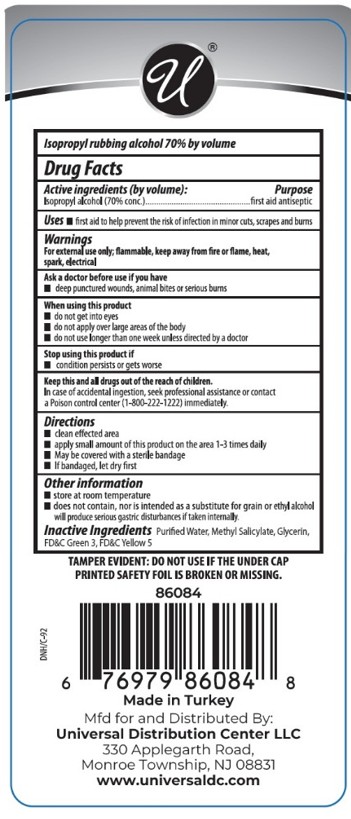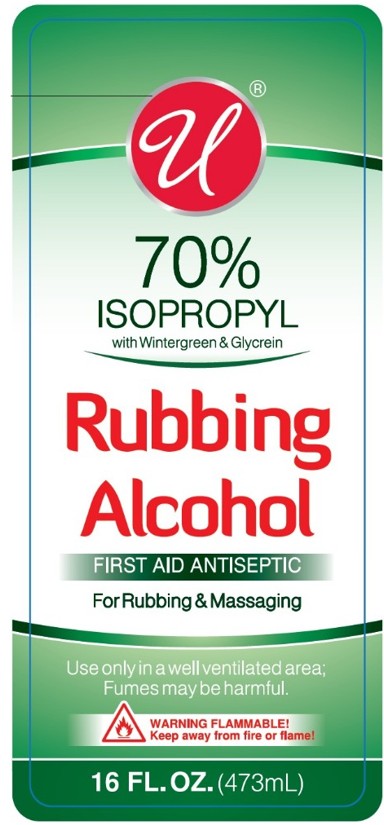 DRUG LABEL: Universal 70% Rubbing Alcohol with Wintergreen and Glycerin
NDC: 76567-4291 | Form: LIQUID
Manufacturer: TSM BRANDS LLC
Category: otc | Type: HUMAN OTC DRUG LABEL
Date: 20250703

ACTIVE INGREDIENTS: ISOPROPYL ALCOHOL 331 mL/473 mL
INACTIVE INGREDIENTS: FD&C GREEN NO. 3; WATER; GLYCERIN; METHYL SALICYLATE; FD&C YELLOW NO. 5

Active Ingredients

Isopropyl alcohol (70% conc.)

PURPOSE

first aid antiseptic

Warnings

For external use only; flammable, keep away from fire or flame, heat, spark, electrical

Ask a doctor before use if you have

deep punctured wounds, animal bites or serious burns

When using this product

• do not get into eyes
• do not apply over large areas of the body
• do not use longer than one week unless directed by a doctor

Stop using this product if

• condition persists or gets worse

Keep this and all drugs out of the reach of children.

In case of accidental ingestion, seek professional assistance or contact a Poison control center (1-800-222-1222) immediately.

Directions

• clean effected area
• apply small amount of this product on the area 1-3 times daily
• May be covered with a sterile bandage
• If bandaged, let dry first

Other information

• store at room temperature
• does not contain, nor is intended as a substitute for grain or ethyl alcohol will produce serious gastric disturbances if taken internally.

Inactive Ingredients

Purified Water, Methyl Salicylate, Glycerin, FD&C Green 3, FD&C Yellow 5

INDICATIONS & USAGE

first aid to help prevent the risk of infection in minor cuts, scrapes and burns